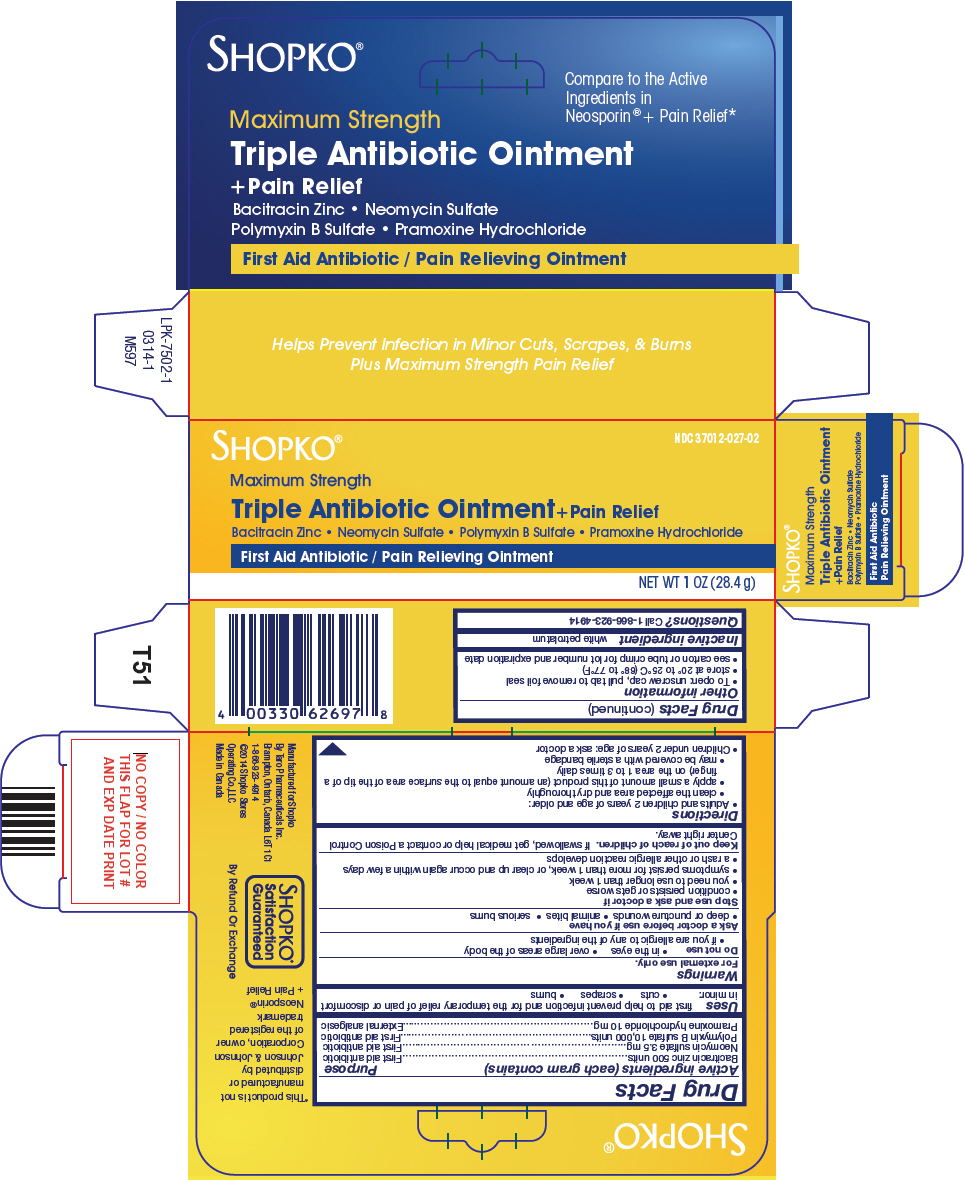 DRUG LABEL: Shopko

NDC: 37012-027 | Form: OINTMENT
Manufacturer: Shopko Stores Operating Co., LLC
Category: otc | Type: HUMAN OTC DRUG LABEL
Date: 20250715

ACTIVE INGREDIENTS: BACITRACIN ZINC 500 [iU]/1 g; NEOMYCIN SULFATE 3.5 mg/1 g; POLYMYXIN B SULFATE 10000 [iU]/1 g; PRAMOXINE HYDROCHLORIDE 10 mg/1 g
INACTIVE INGREDIENTS: PETROLATUM

Shopko®
Triple Antibiotic plus Pain Relief

Drug Facts

ACTIVE INGREDIENT

Active ingredients (each gram contains) | Purpose
Bacitracin zinc 500 units | First aid antibiotic
Neomycin sulfate 3.5 mg | First aid antibiotic
Polymyxin B sulfate 10,000 units | First aid antibiotic
Pramoxine hydrochloride 10 mg | External analgesic

Uses

first aid to help prevent infection and for the temporary relief of pain or discomfort in minor:

- cuts
- scrapes
- burns

Warnings

For external use only.

Do not use

- in the eyes
- over large areas of the body
- if you are allergic to any of the ingredients

Ask a doctor before use if you have

- deep or puncture wounds
- animal bites
- serious burns

Stop use and ask a doctor if

- condition persists or gets worse
- you need to use longer than 1 week
- symptoms persist for more than 1 week, or clear up and occur again within a few days
- a rash or other allergic reaction develops

Keep out of reach of children.If swallowed, get medical help or contact a Poison Control Center right away.

Directions

- Adults and children 2 years of age and older:
  - clean the affected area and dry thoroughly
  - apply a small amount of this product (an amount equal to the surface area of the tip of a finger) on the area 1 to 3 times daily
  - may be covered with a sterile bandage
- Children under 2 years of age: ask a doctor

Other information

- To open: unscrew cap, pull tab to remove foil seal
- store at 20° to 25°C (68° to 77°F)
- see carton or tube crimp for lot number and expiration date

Inactive ingredient

white petrolatum

Questions?

Call 1-866-923-4914

PRINCIPAL DISPLAY PANEL - 28.4 g Tube Carton

SHOPKO®

NDC 37012-027-02

Maximum Strength
Triple Antibiotic Ointment+Pain Relief
Bacitracin Zinc • Neomycin Sulfate • Polymyxin B Sulfate • Pramoxine Hydrochloride

First Aid Antibiotic / Pain Relieving Ointment

NET WT 1OZ (28.4 g)